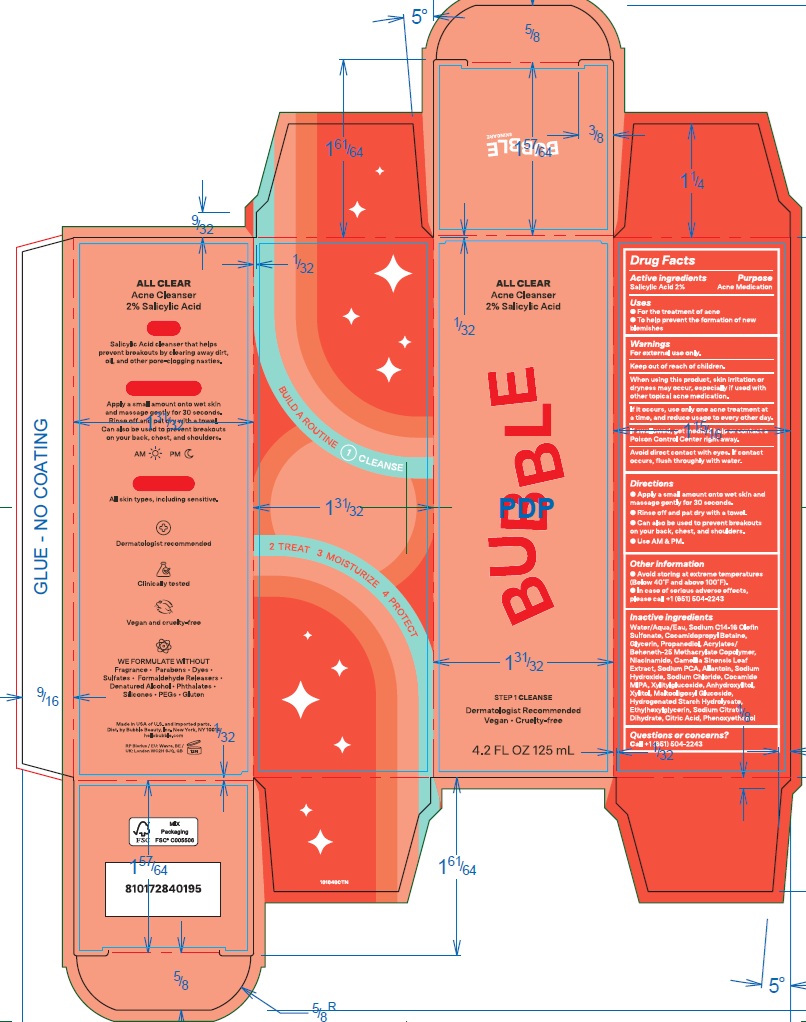 DRUG LABEL: Bubble All Clear Acne Cleanser
NDC: 83509-004 | Form: EMULSION
Manufacturer: BUBBLE BEAUTY
Category: otc | Type: HUMAN OTC DRUG LABEL
Date: 20250826

ACTIVE INGREDIENTS: SALICYLIC ACID 20 mg/1 mL
INACTIVE INGREDIENTS: SODIUM C14-16 OLEFIN SULFONATE; COCAMIDOPROPYL BETAINE; CAMELLIA SINENSIS LEAF; SODIUM PCA; SODIUM CHLORIDE; NIACINAMIDE; ALLANTOIN; COCAMIDE MIPA; XYLITYLGLUCOSIDE; ANHYDROXYLITOL; XYLITOL; MALTOOLIGOSYL GLUCOSIDE; HYDROGENATED STARCH HYDROLYSATE; CITRIC ACID MONOHYDRATE; SODIUM HYDROXIDE; WATER; ETHYLHEXYLGLYCERIN; GLYCERIN; PROPANEDIOL; TRISODIUM CITRATE DIHYDRATE; PHENOXYETHANOL

Bubble All Clear Acne Cleanser

Active ingredients

Salicylic Acid 2%

Purpose

Acne Medication

Uses

- For the treatment of acne
- To help prevent the formation of new blemishes

Warnings

For external use only.

When using this product

- skin irritation or dryness may occur, especially if used with other topical acne medication. If it occurs, use only one acne treatment at a time, and reduce usage to every other day.
- avoid direct contact with eyes. If contact occurs, flush thoroughly with water.

Keep out of reach of children.

If swallowed, get medical help or contact a Poison Control Center right away.

Directions

- Apply a small amount onto wet skin and massage gently for 30 seconds.
- Rinse off and pat dry with a towel.
- Can also be used to prevent breakouts on your back, chest, and shoulders.
- Use AM & PM.

Other information

- Avoid storing at extreme temperatures (Below 40F and above 100F).
- In case of serious adverse effects, please call +1(651) 504-2243

Inactive ingredients

Water/Aqua/Eau, Sodium C14-16 Olefin Sulfonate, Cocamidopropyl Betaine, Glycerin, Propanediol, Acrylates/Beheneth-25 Methacrylates Copolymer, Niacinamide, Camellia Sinensis Leaf Extract, Sodium PCA, Allantoin, Sodium Hydroxide, Sodium Chloride, Cocamide MIPA, Xylitylglucoside, Anhydroxylitol, Xylitol, Maltooligosyl Glucoside, Hydrogenated Starch Hydrolysate, Ethylhexylglycerin, Sodium Citrate Dihydrate, Citric Acid, Phenoxyethanol

Questions or concerns?

Call +1 (651) 504-2243